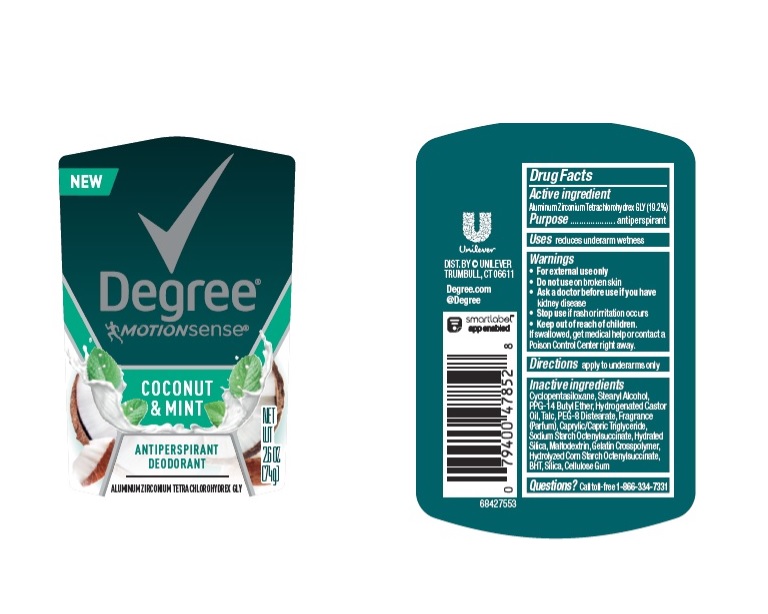 DRUG LABEL: Degree
NDC: 64942-1789 | Form: STICK
Manufacturer: Conopco Inc. d/b/a/ Unilever
Category: otc | Type: HUMAN OTC DRUG LABEL
Date: 20241110

ACTIVE INGREDIENTS: ALUMINUM ZIRCONIUM TETRACHLOROHYDREX GLY 19.2 g/100 g
INACTIVE INGREDIENTS: HYDRATED SILICA; CYCLOMETHICONE 5; HYDROGENATED CASTOR OIL; BUTYLATED HYDROXYTOLUENE; PPG-14 BUTYL ETHER; STEARYL ALCOHOL; MALTODEXTRIN; SILICON DIOXIDE; CARBOXYMETHYLCELLULOSE SODIUM, UNSPECIFIED FORM; TALC; PEG-8 DISTEARATE; MEDIUM-CHAIN TRIGLYCERIDES

Degree Motionsense Coconut & Mango Antiperspirant Deodorant

DEGREE MOTIONSENSE COCONUT & MANGO ANTIPERSPIRANT DEODORANT - aluminum zirconium tetrachlorohydrex gly

Degree Motionsense Coconut & Mango Antiperspirant Deodorant

Drug Facts

Active ingredient

Aluminum Zirconium Tetrachlorohydrex GLY (19.2 %)

Purpose

antiperspirant

Uses

reduces underarm wetness

Warnings

• For external use only.
• Do not use on broken skin .
• Ask a doctor before use if you have kidney disease.
• Stop use if rash or irritation occurs.

• Keep out of reach of children.

If swallowed, get medical help or contact a Poison Control Center right away.

Directions

apply to underarms only

Inactive ingredients

Cyclopentasiloxane, Stearyl Alcohol, PPG-14 Butyl Ether, Hydrogenated Castor Oil, Talc, PEG-8 Distearate, Fragrance (Parfum), Caprylic/Capric Triglyceride, Sodium Starch Octenylsuccinate, Hydrated Silica, Maltodextrin, Gelatin Crosspolymer, Hydrolyzed Corn Starch Octenylsuccinate, BHT, Silica, Cellulose Gum

Questions?

Call toll-free 1-866-334-7331